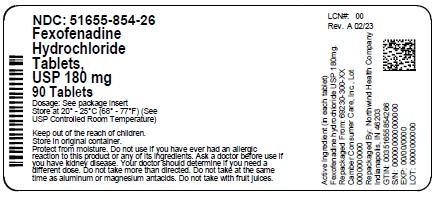 DRUG LABEL: Fexofenadine HCL
NDC: 51655-854 | Form: TABLET
Manufacturer: Northwind Health Company, LLC
Category: otc | Type: HUMAN OTC DRUG LABEL
Date: 20260101

ACTIVE INGREDIENTS: FEXOFENADINE HYDROCHLORIDE 180 mg/1 1
INACTIVE INGREDIENTS: SILICON DIOXIDE; HYPROMELLOSE 2910 (6 MPA.S); LIGHT MINERAL OIL; MAGNESIUM STEARATE; CELLULOSE, MICROCRYSTALLINE; POLYSORBATE 80; STARCH, CORN; FERRIC OXIDE RED; FERRIC OXIDE YELLOW; SODIUM STARCH GLYCOLATE TYPE A POTATO; TALC; TITANIUM DIOXIDE; POLYETHYLENE GLYCOL 6000

Fexofenadine Hydrochloride Tablets USP, 180 mg

ACTIVE INGREDIENT(S), in each tablet

Fexofenadine hydrochloride USP, 180 mg

PURPOSE

Antihistamine

USE(S)

temporarily relieves these symptoms due to hay fever or other upper respiratory allergies:

§ runny nose

§ sneezing

§ itchy, watery eyes

§ itching of the nose or throat

DO NOT USE

if you have ever had an allergic reaction to this product or any of its ingredients.

ASK A DOCTOR BEFORE USE IF

you have kidney disease. Your doctor should determine if you need a different dose.

WHEN USING THIS PRODUCT

§ do not take more than directed

§ do not take at the same time as aluminum or magnesium antacids

§ do not take with fruit juices (see Directions)

STOP USE AND ASK A DOCTOR IF

an allergic reaction to this product occurs. Seek medical help right away.
If pregnant or breast-feeding, ask a health professional before use.

KEEP OUT OF REACH OF CHILDREN

In case of overdose, get medical help or contact a Poison Control Center right away.

DIRECTIONS

60 mg

adults and children 12 years of age and over | take one 60 mg tablet with water every 12 hours; do not take more than 2 tablets in 24 hours
children under 12 years of age | do not use
adults 65 years of age and older | ask a doctor
consumers with kidney disease | ask a doctor

180 mg

adults and children 12 years of age and over | take one 180 mg tablet with water once a day; do not take more than 1 tablet in 24 hours
children under 12 years of age | do not use
adults 65 years of age and older | ask a doctor
consumers with kidney disease | ask a doctor

OTHER INFORMATION

-  Safety Sealed: do not use if carton is opened or if printed foil inner seal on the bottle is torn or missing.
-  store between 20° and 25°C (68° and 77°F)
-  protect from excessive moisture

INACTIVE INGREDIENTS

Colloidal silicon dioxide, hypromellose, light liquid paraffin, magnesium stearate, microcrystalline cellulose, polyethylene glycol, polysorbate 80, pregelatinized starch, red iron oxide, sodium starch glycolate, talc, titanium dioxide and yellow iron oxide.

QUESTIONS OR COMMENTS

call toll-free weekdays 9 AM to 5 PM EST at 1-888-588-1418

PRINCIPAL DISPLAY PANEL

NDC: 51655-854-26